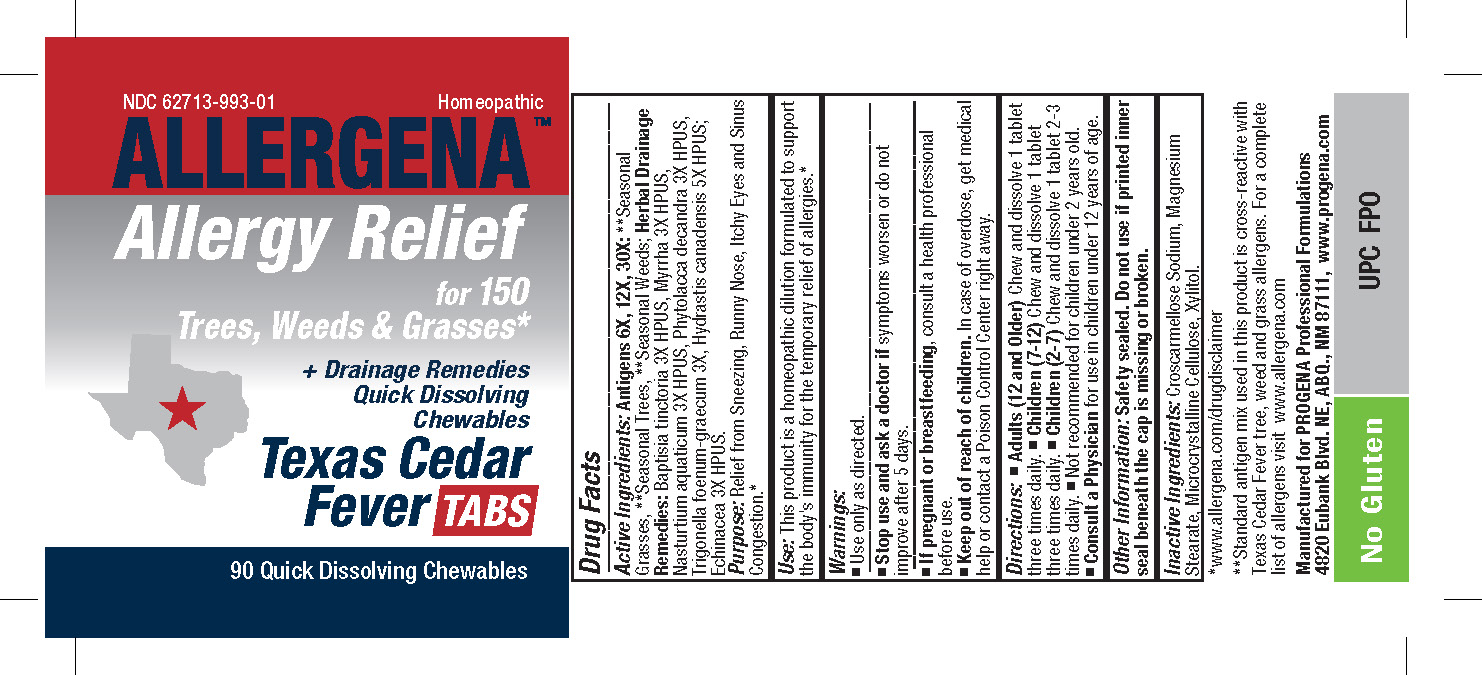 DRUG LABEL: Allergena Texas Cedar Fever Tabs
NDC: 62713-993 | Form: TABLET, ORALLY DISINTEGRATING
Manufacturer: Meditrend, Inc. DBA Progena Professional Formulations
Category: homeopathic | Type: HUMAN OTC DRUG LABEL
Date: 20250129

ACTIVE INGREDIENTS: QUERCUS ALBA POLLEN 30 [hp_X]/1 1; CARYA ILLINOINENSIS POLLEN 30 [hp_X]/1 1; PINUS STROBUS POLLEN 30 [hp_X]/1 1; POPULUS ALBA POLLEN 30 [hp_X]/1 1; LIQUIDAMBAR STYRACIFLUA POLLEN 30 [hp_X]/1 1; PLATANUS OCCIDENTALIS POLLEN 30 [hp_X]/1 1; JUGLANS NIGRA POLLEN 30 [hp_X]/1 1; SALIX NIGRA POLLEN 30 [hp_X]/1 1; BACCHARIS HALIMIFOLIA POLLEN 30 [hp_X]/1 1; AMARANTHUS PALMERI POLLEN 30 [hp_X]/1 1; XANTHIUM STRUMARIUM POLLEN 30 [hp_X]/1 1; RUMEX CRISPUS POLLEN 30 [hp_X]/1 1; CHENOPODIUM ALBUM POLLEN 30 [hp_X]/1 1; IVA ANNUA POLLEN 30 [hp_X]/1 1; ARTEMISIA VULGARIS POLLEN 30 [hp_X]/1 1; URTICA DIOICA POLLEN 30 [hp_X]/1 1; AMARANTHUS RETROFLEXUS POLLEN 30 [hp_X]/1 1; PLANTAGO LANCEOLATA POLLEN 30 [hp_X]/1 1; AMBROSIA TRIFIDA POLLEN 30 [hp_X]/1 1; AMBROSIA ARTEMISIIFOLIA POLLEN 30 [hp_X]/1 1; PASPALUM NOTATUM POLLEN 30 [hp_X]/1 1; CYNODON DACTYLON POLLEN 30 [hp_X]/1 1; POA PRATENSIS POLLEN 30 [hp_X]/1 1; FESTUCA PRATENSIS POLLEN 30 [hp_X]/1 1; SORGHUM HALEPENSE POLLEN 30 [hp_X]/1 1; LOLIUM PERENNE POLLEN 30 [hp_X]/1 1; DACTYLIS GLOMERATA POLLEN 30 [hp_X]/1 1; AGROSTIS GIGANTEA POLLEN 30 [hp_X]/1 1; BAPTISIA TINCTORIA ROOT 3 [hp_X]/1 1; GOLDENSEAL 5 [hp_X]/1 1; MYRRH 3 [hp_X]/1 1; NASTURTIUM OFFICINALE 3 [hp_X]/1 1; PHYTOLACCA AMERICANA ROOT 3 [hp_X]/1 1; FENUGREEK LEAF 3 [hp_X]/1 1; ECHINACEA, UNSPECIFIED 3 [hp_X]/1 1; ACACIA POLLEN 30 [hp_X]/1 1; ALNUS RUBRA POLLEN 30 [hp_X]/1 1; ALNUS INCANA SUBSP. RUGOSA POLLEN 30 [hp_X]/1 1; FRAXINUS VELUTINA POLLEN 30 [hp_X]/1 1; FRAXINUS PENNSYLVANICA POLLEN 30 [hp_X]/1 1; FRAXINUS AMERICANA POLLEN 30 [hp_X]/1 1; POPULUS TREMULOIDES POLLEN 30 [hp_X]/1 1; MORELLA CERIFERA POLLEN 30 [hp_X]/1 1; FAGUS GRANDIFOLIA POLLEN 30 [hp_X]/1 1; BETULA PAPYRIFERA POLLEN 30 [hp_X]/1 1; BETULA NIGRA POLLEN 30 [hp_X]/1 1; BETULA LENTA POLLEN 30 [hp_X]/1 1; ROBINIA PSEUDOACACIA POLLEN 30 [hp_X]/1 1; ACER NEGUNDO POLLEN 30 [hp_X]/1 1; JUNIPERUS ASHEI POLLEN 30 [hp_X]/1 1; JUNIPERUS PINCHOTII POLLEN 30 [hp_X]/1 1; JUNIPERUS VIRGINIANA POLLEN 30 [hp_X]/1 1; POPULUS DELTOIDES SUBSP. DELTOIDES POLLEN 30 [hp_X]/1 1; POPULUS DELTOIDES SUBSP. MONILIFERA POLLEN 30 [hp_X]/1 1; CUPRESSUS ARIZONICA POLLEN 30 [hp_X]/1 1; TAXODIUM DISTICHUM POLLEN 30 [hp_X]/1 1; PHOENIX DACTYLIFERA POLLEN 30 [hp_X]/1 1; ULMUS AMERICANA POLLEN 30 [hp_X]/1 1; ULMUS CRASSIFOLIA POLLEN 30 [hp_X]/1 1; ULMUS PUMILA POLLEN 30 [hp_X]/1 1; ULMUS RUBRA POLLEN 30 [hp_X]/1 1; EUCALYPTUS GLOBULUS POLLEN 30 [hp_X]/1 1; PSEUDOTSUGA MENZIESII POLLEN 30 [hp_X]/1 1; CELTIS OCCIDENTALIS POLLEN 30 [hp_X]/1 1; CARYA GLABRA POLLEN 30 [hp_X]/1 1; CARYA OVATA POLLEN 30 [hp_X]/1 1; CARYA LACINIOSA POLLEN 30 [hp_X]/1 1; CARYA ALBA POLLEN 30 [hp_X]/1 1; LIGUSTRUM VULGARE POLLEN 30 [hp_X]/1 1; ACER SACCHARUM POLLEN 30 [hp_X]/1 1; ACER RUBRUM POLLEN 30 [hp_X]/1 1; MORUS RUBRA POLLEN 30 [hp_X]/1 1; QUERCUS VIRGINIANA POLLEN 30 [hp_X]/1 1; QUERCUS RUBRA POLLEN 30 [hp_X]/1 1
INACTIVE INGREDIENTS: XYLITOL; CROSCARMELLOSE SODIUM; MAGNESIUM STEARATE; CELLULOSE, MICROCRYSTALLINE

Allergena Texas Cedar Fever Tabs

ACTIVE INGREDIENT

Active Ingredients:Antigens 6X, 12X, 30X: **Seasonal Grasses, **Seasonal Trees, **Seasonal Weeds; Herbal Drainage Remedies: Baptisia tinctoria 3X HPUS, Myrrha 3X HUPS, Nasturtium aquaticum 3X HPUS, Phytolacca decandra 3X HPUS, Trigonella foenum-graecum 3X, Hydrastis canadensis 5X HPUS; Echinacea 3X HPUS.

PURPOSE

Purpose:Relief from Sneezing, Runny Nose, Itchy Eyes and Sinus Congestion.*

Keep Out of Reach of Children.In case of overdose, get medical help or contact a Poison Control Center right away.

INDICATIONS AND USAGE

Use: This product is a Homeopathic dilution formulated to support the body's immunity for the temporary relief of allergies.*

Warnings:

- Use only as directed.
- Stop use and ask a doctor ifsymptoms worsen or do not improve after 5 days.
- If pregnant or breastfeeding, consult a health professional before use.

DOSAGE AND ADMINISTRATION

Directions: •Adults (12 and Older) Chew and dissolve 1 tablet three times daily. • Children (7-12) Chew and dissolve 1 tablet three times daily. • Children (2-7) Chew and dissolve 1 tablet 2-3 times daily. • Not recommended for children under 2 years old. • Consult a Physician for use in children under 12 years of age.

Other Information:Safety sealed. Do not use if printed inner seal beneath the cap is missing or broken.

INACTIVE INGREDIENT

Inactive Ingredients:Croscarmellose Sodium, MagnesiumStearate, Microcrystalline Cellulose, Xylitol.

PACKAGE LABEL

*www.allergena.com/disclaimer
**Standard antigen mix used inthes product is cross-reactive with Texas Cedar Fever tree, weed, and grass allergens. For a complete list of allergens visit www.allergena.com

Manufactured for PROGENA Professional Formulations
4820 Eubank Blvd. NE, ABQ, NM 87111, www.progena.com